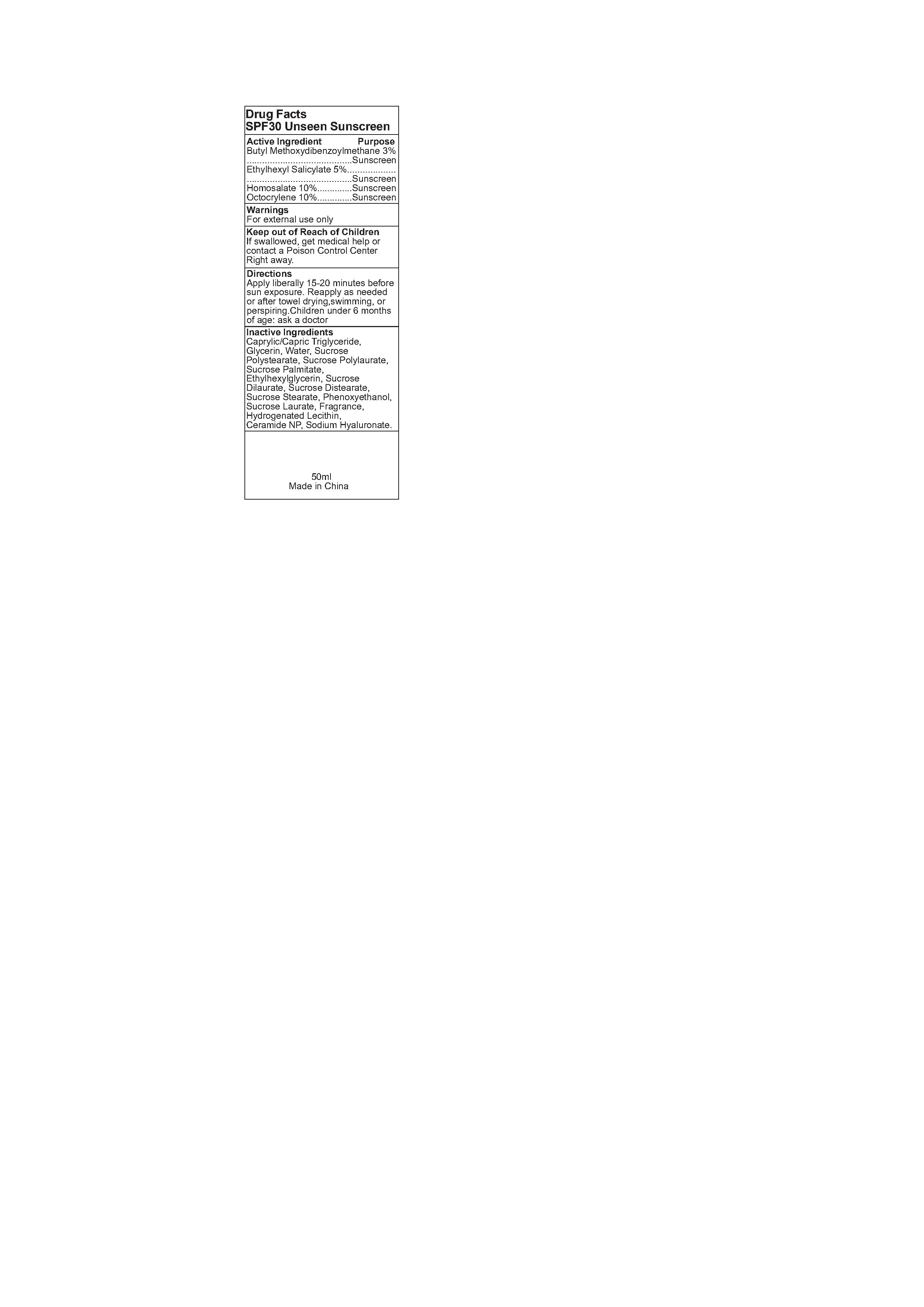 DRUG LABEL: SPF30 unseen sunscreen
NDC: 82953-046 | Form: CREAM
Manufacturer: Cosmuses Cosmetics (Ningbo) Co., Ltd.
Category: otc | Type: HUMAN OTC DRUG LABEL
Date: 20250709

ACTIVE INGREDIENTS: BUTYL METHOXYDIBENZOYLMETHANE 3 g/100 mL; HOMOSALATE 10 g/100 mL; OCTOCRYLENE 10 g/100 mL; ETHYLHEXYL SALICYLATE 5 g/100 mL
INACTIVE INGREDIENTS: HYDROGENATED SOYBEAN LECITHIN; GLYCERIN; PHENOXYETHANOL; WATER; SUCROSE POLYSTEARATE; SUCROSE LAURATE; FRAGRANCE 13576; SUCROSE DILAURATE; CERAMIDE NP; SODIUM HYALURONATE; CAPRYLIC/CAPRIC TRIGLYCERIDE; SUCROSE PALMITATE; ETHYLHEXYLGLYCERIN; ACETYLATED SUCROSE DISTEARATE; SUCROSE STEARATE

REEF SAFE Unscented SPF 50 Mineral Sunscreen

Drug Facts

Active ingredients

Butyl Methoxydibenzoylmethane 3%

Ethylhexyl Salicylate 5%

Homosalate 10%

Octocrylene 10%

Purpose

Sunscreen

Warnings

For external use only.

Keep out of Reach of Children

If swallowed, get medical help or contact a Poison Control Center Right away.

Directions

Apply liberally 15-20 minutes before sun exposure. Reapply as needed or after towel drying, swimming, or perspiring. Children under 6 months of age: ask a doctor

INDICATIONS AND USAGE

Reapply as needed or after towel drying, swimming, or perspiring.

Inactive ingredients

Caprylic/Capric Triglyceride, Glycerin, Water, Sucrose Polystearate, Sucrose Polylaurate, Sucrose Palmitate, Ethylhexylglycerin, Sucrose Dilaurate, Sucrose Distearate, Sucrose Stearate, Fragrance, Hydrogenated Lecithin, Ceramide NP, Sodium Hyaluronate.